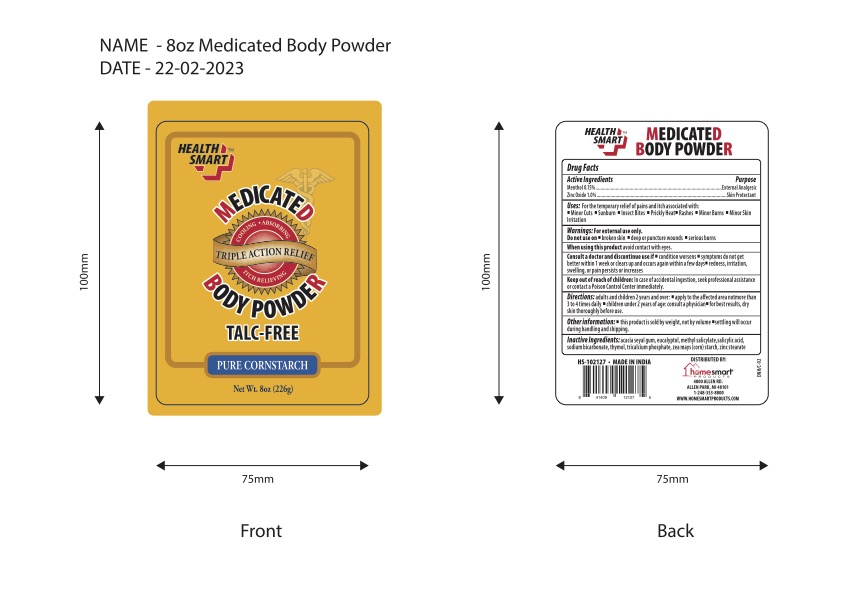 DRUG LABEL: Health Smart Medicated Body
NDC: 52862-030 | Form: POWDER
Manufacturer: International Wholesale Inc dba Home Smart Products
Category: otc | Type: HUMAN OTC DRUG LABEL
Date: 20241219

ACTIVE INGREDIENTS: MENTHOL 0.15 g/100 g; ZINC OXIDE 1 g/100 g
INACTIVE INGREDIENTS: TRICALCIUM PHOSPHATE; SODIUM BICARBONATE; SALICYLIC ACID; ACACIA; EUCALYPTUS OIL; METHYL SALICYLATE; THYMOL; ZINC STEARATE; ZEA MAYS SUBSP. MAYS WHOLE

Health Smart Medicated Body Powder (Talc Free)

Active Ingredients

Menthol 0.15%

Zinc Oxide 1.0%

Purpose

External Analgesic

Skin Protectant

Uses

For the temporary relief of pains and itch associated with:

- Minor Cuts
- Scrapes
- Sunburn
- Insect Bites
- Prickly Heat
- Rashes
- Minor Burns
- Minor Skin Irritation
- Dries the oozing of poison ivy, oak, and sumac.

Warnings

For external use only.

When using this productavoid contact with eyes.

Consult a doctor and discontinue use if

- condition worsens
- symptoms do not get better within 1 week or clear up and occurs again within a few days.

Keep out of reach of children

In case of accidental ingestion, seek professional assistance or contact a Poison Control Center immediately.

Directions

adults and children 2 years and over

- apply to the affected area not more than 3 or 4 times daily.
- children under 2 years of age: consult a physician.
- for best results, dry skin thoroughly before use.

Inactive Ingredients

acacia seyal gum, eucalyptus oil, methyl salicylate, salicylic acid, sodium bicarbonate, thymol, tricalcium phosphate, zea mays (corn starch) zinc stearate.

PRINCIPAL DISPLAY PANEL

HEALTH SMART MEDICATED BODY POWDER

NET WT. 10 OZ. (283g)